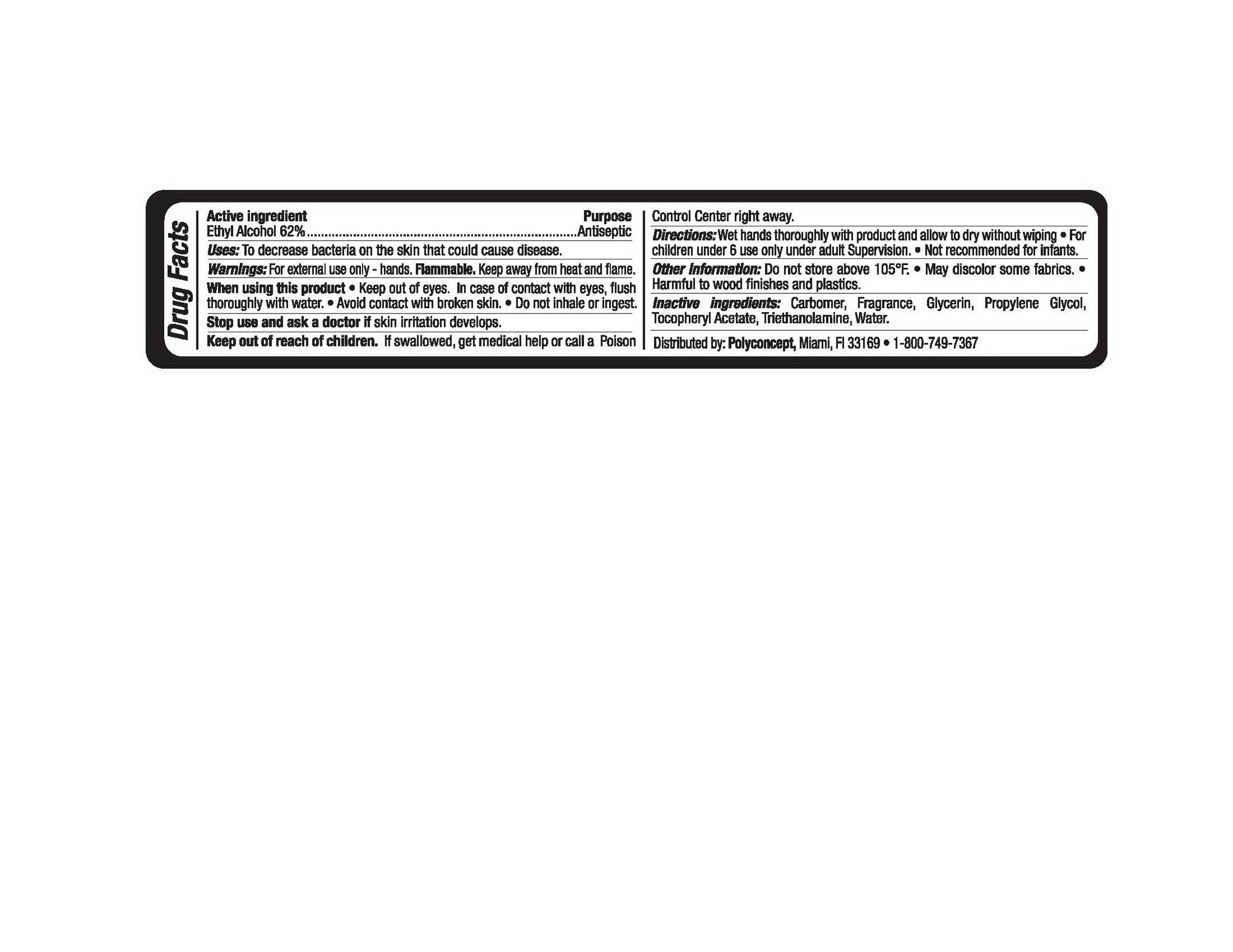 DRUG LABEL: Hand Sanitizer
NDC: 52174-002 | Form: LIQUID
Manufacturer: Ningbo Kleen Products Co., Ltd.
Category: otc | Type: HUMAN OTC DRUG LABEL
Date: 20100908

ACTIVE INGREDIENTS: ALCOHOL 62 g/100 g
INACTIVE INGREDIENTS: WATER 36.43 g/100 g; ALPHA-TOCOPHEROL ACETATE 0.02 g/100 g; CARBOMER HOMOPOLYMER TYPE C 0.2 g/100 g; TROLAMINE 0.2 g/100 g; GLYCERIN 0.5 g/100 g; PROPYLENE GLYCOL 0.5 g/100 g

Label Content

Active Ingredient: Ethyl Alcohol 62%

Purpose: Antiseptic

INDICATIONS AND USAGE

Uses: To decrease bacteria on the skin that could cause disease

WARNINGS

Warnings: For external use only-hands. Flammable. Keep away from heat and flame.
When using this product. Keep out of eyes. In case of contact with eyes, flush thoroughly with water. Avoid contact with broken skin. Do not inhale or ingest

Stop use and see a doctor if skin irritation develops.

Keep out of reach of children. If swallowed, get medical help or call a poison control center right away

INACTIVE INGREDIENT

Carbomer, Fragrance, Glycerin, Propylene Glycol, Tocopheryl Acetate, Triethanolamine, Water

Other Information
Do not store above 105F
May discolor some fabric
Harmful to wood finishes and plastics

DOSAGE AND ADMINISTRATION

Directions: Wet hands thoroughly with products and allow to dry without wiping. For children under 6 use only under adult supervision. Not recommended for infants

PACKAGE LABEL

labe